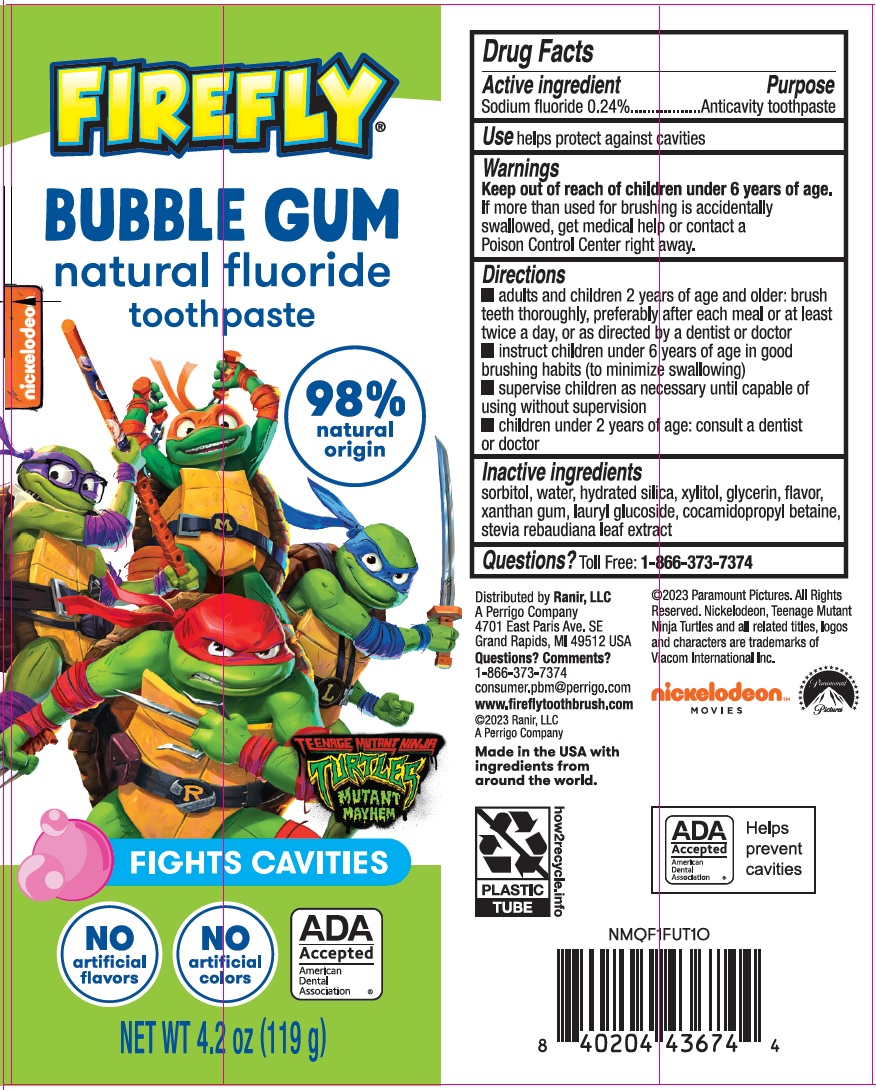 DRUG LABEL: Firefly Bubble Gum natural fluoride
NDC: 66923-323 | Form: PASTE, DENTIFRICE
Manufacturer: Ranir LLC
Category: otc | Type: HUMAN OTC DRUG LABEL
Date: 20241125

ACTIVE INGREDIENTS: SODIUM FLUORIDE 0.24 g/100 g
INACTIVE INGREDIENTS: SORBITOL; WATER; HYDRATED SILICA; XYLITOL; GLYCERIN; XANTHAN GUM; LAURYL GLUCOSIDE; COCAMIDOPROPYL BETAINE; STEVIA REBAUDIUNA LEAF

FIREFLY® TEENAGE MUTANT NINJA TURTLES BUBBLE GUM NATURAL FLUORIDE TOOTHPASTE Drug Facts

Active ingredient

Sodium Fluoride 0.24%

Purpose

Anticavity toothpaste

Use

helps protect against cavities

Warnings

Keep out of reach of children under 6 years of age.

If more than used for brushing is accidentally swallowed, get medical help or contact a Poison Control Center right away.

Directions

- adults and children 2 years of age and older: brush teeth thoroughly, preferable after each meal or at least twice a day, or as directed by a dentist or doctor
- instruct children under 6 years of age in good brushing and rinsing habits (to minimize swallowing)
- supervise children as necessary until capable of using without supervision
- children under 2 years of age: consult a dentist or doctor

Inactive ingredients

sorbitol, water, hydrated silica, zylitol, glycerin, flavor, xanthan gum, lauryl glucoside, cocamidopropyl betaine, stevia rebaudiana extract

Questions?

Toll Free: 1-866-373-7374

Package/Label Principal Display Panel

FIREFLY®

BUBBLE GUM natural fluoride toothpaste

nickelodeon™

98% natural origin

TEENAGE MUTANT NINJA TURTLES

MUTANT MAYHEM

FIGHTS CAVITIES

NO artificial flavors

NO artificial colors

ADA Accepted American Dental Association®

NET WT 4.2 oz (119 g)